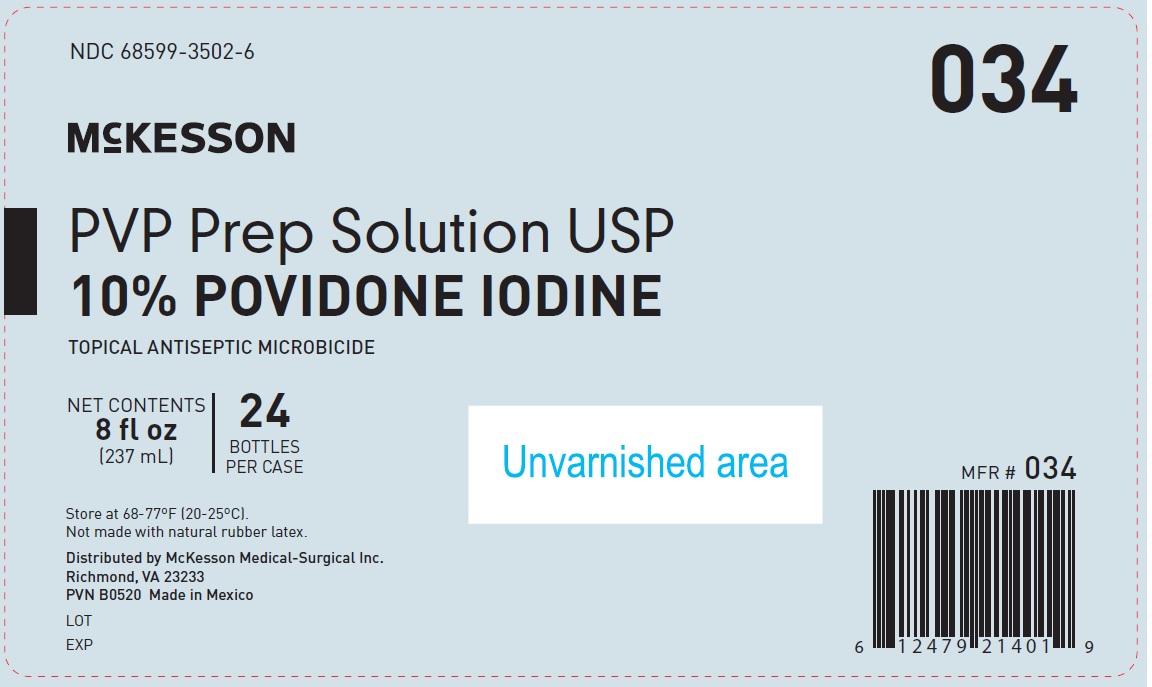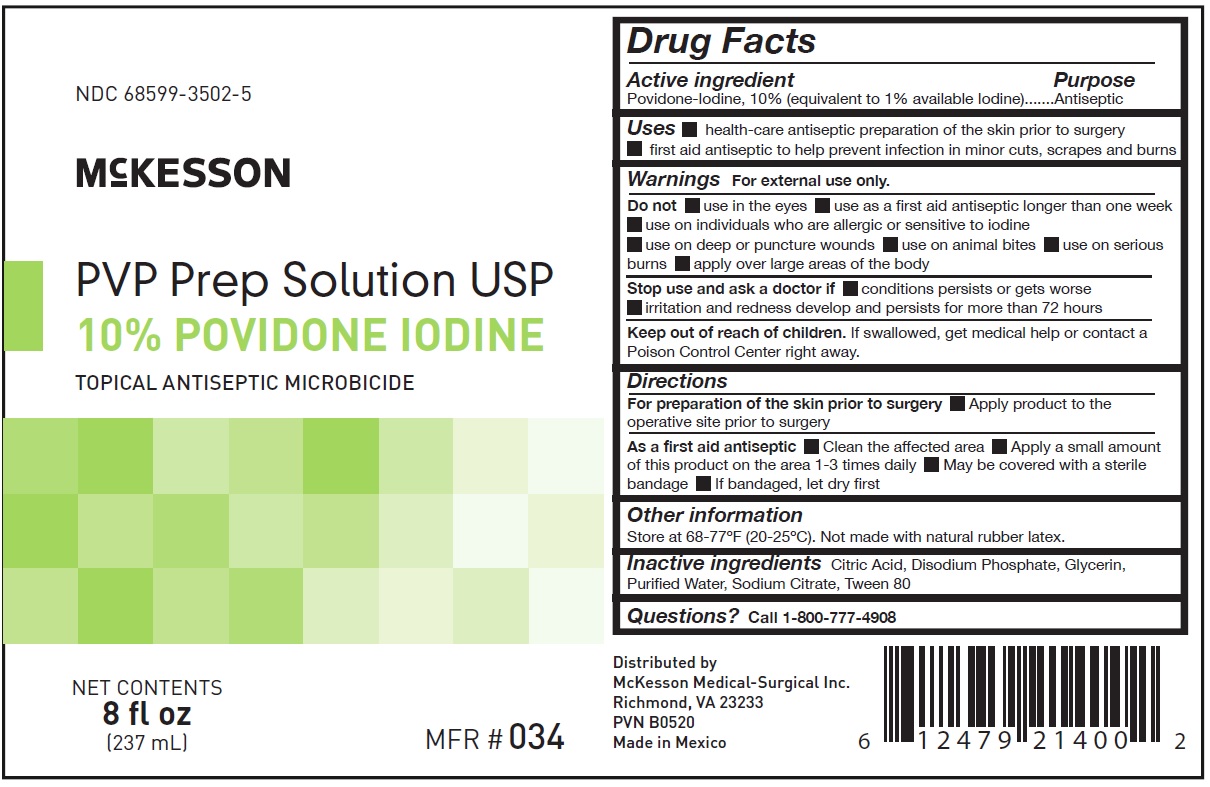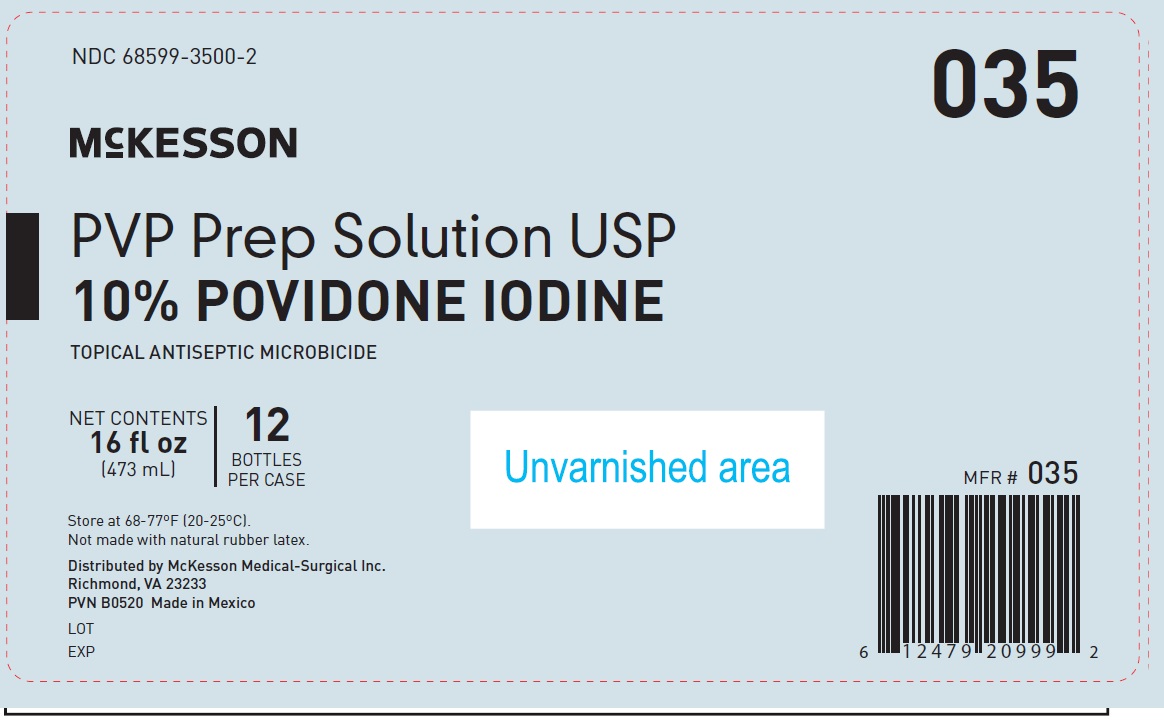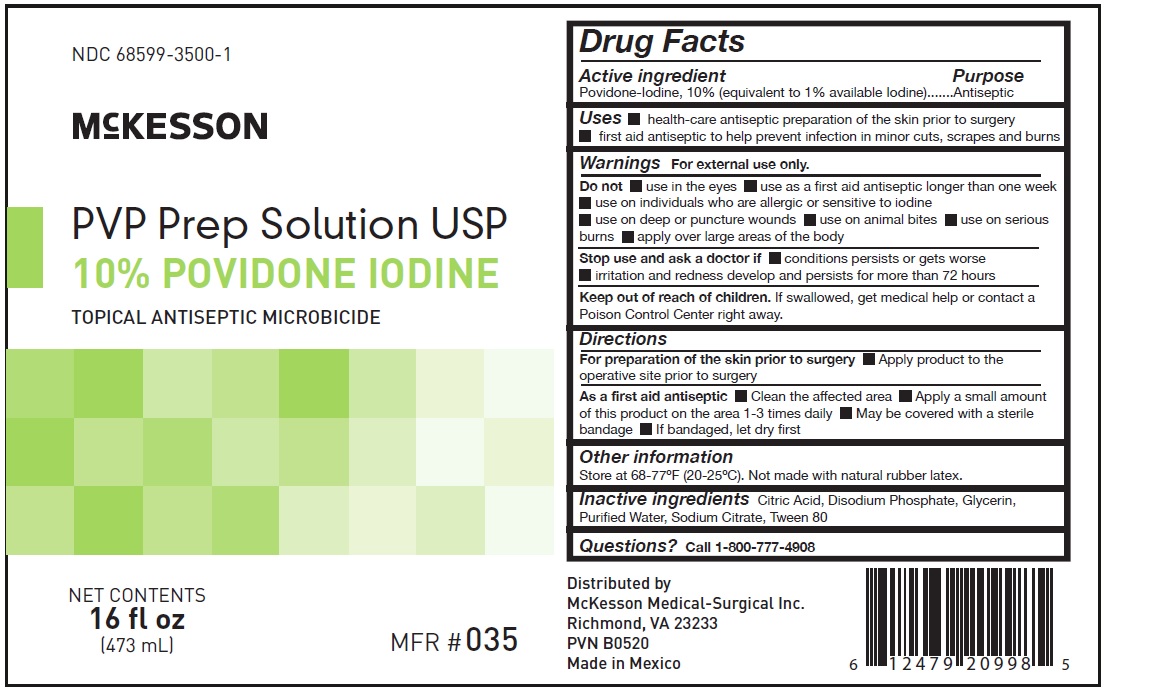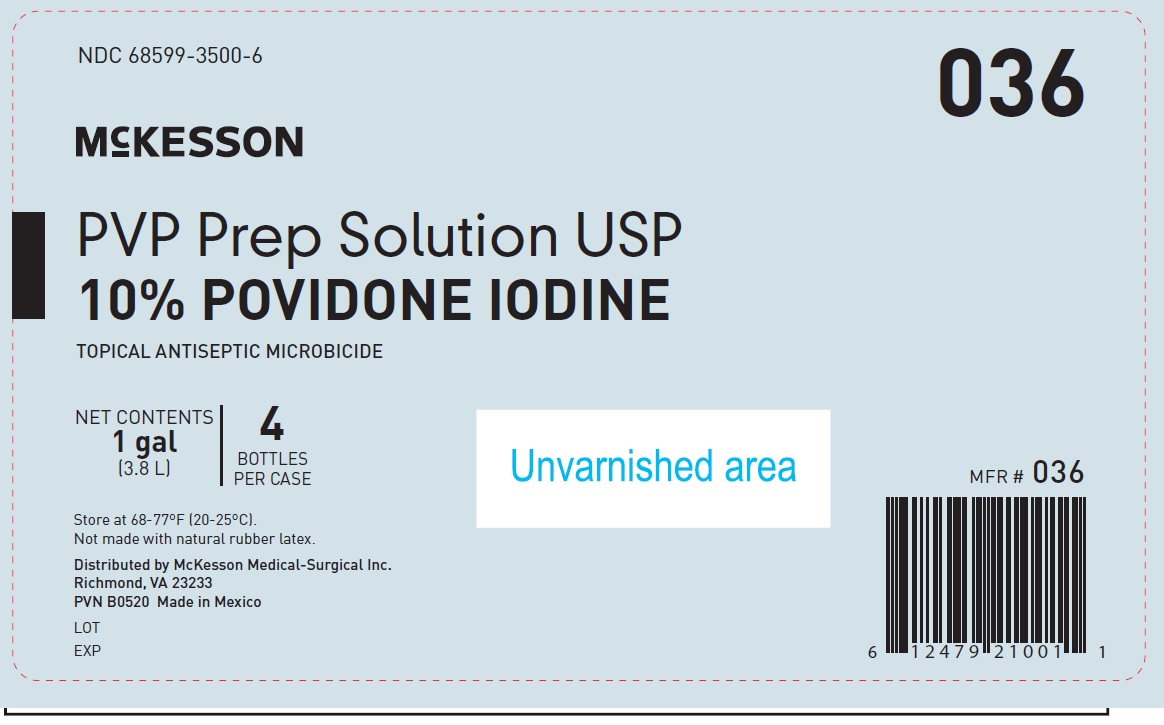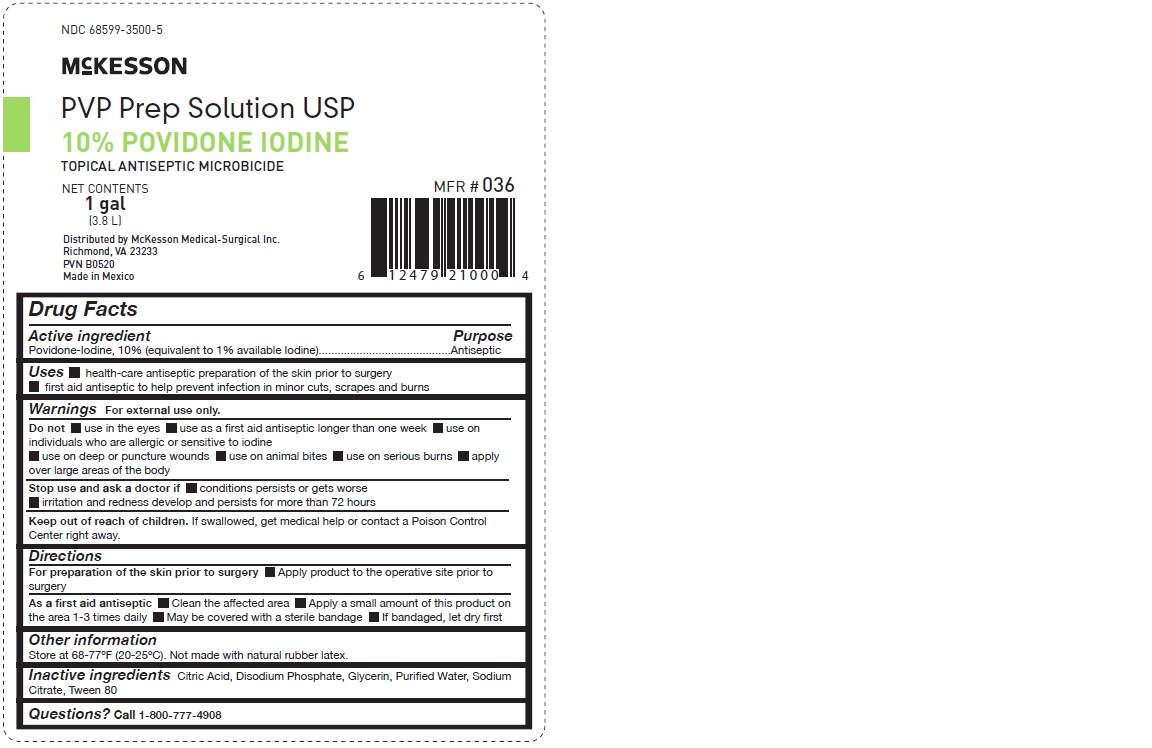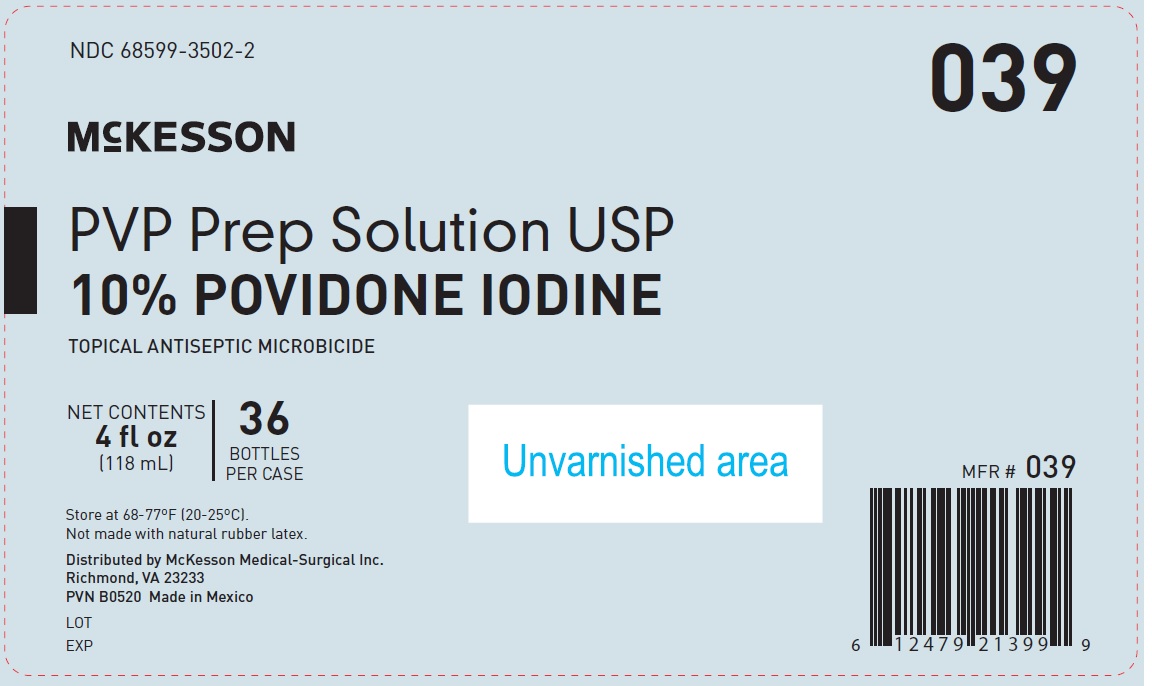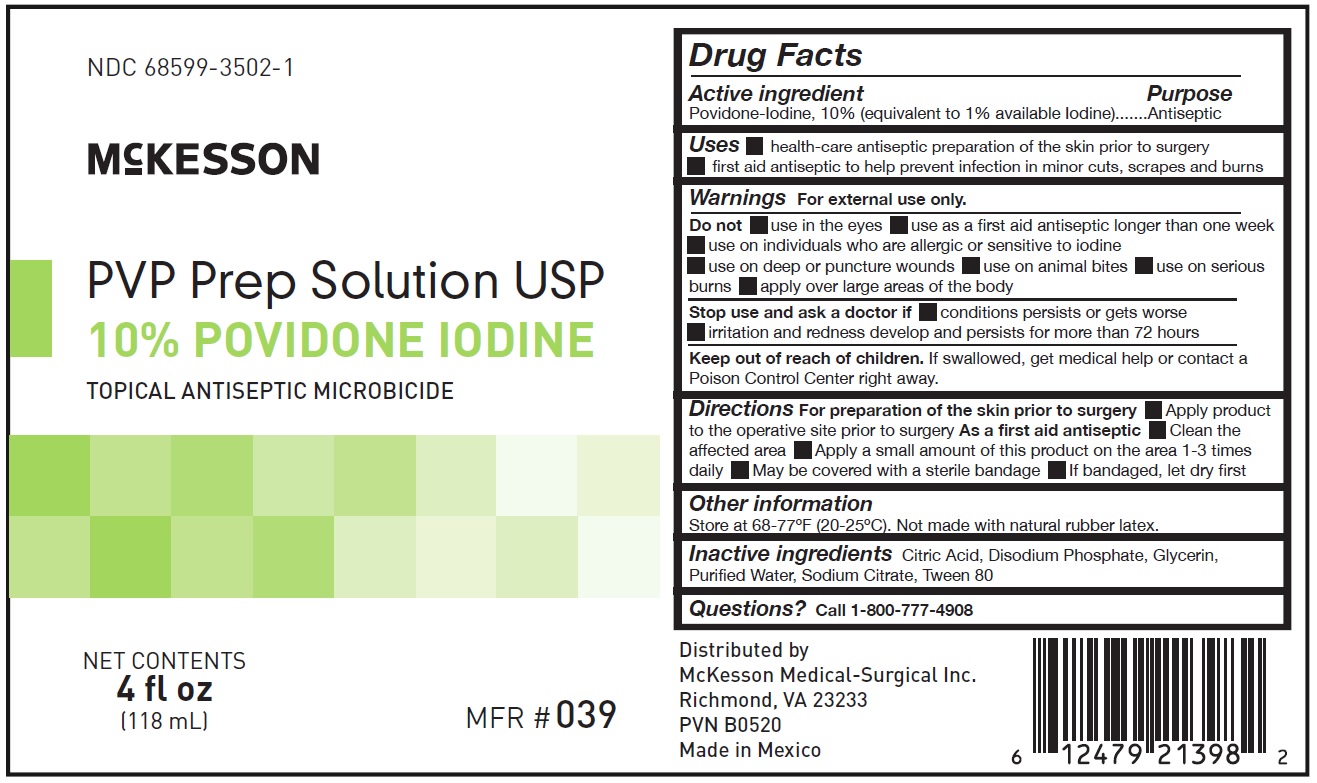 DRUG LABEL: McKesson PVP Prep
NDC: 68599-3502 | Form: LIQUID
Manufacturer: McKesson Medical-Surgical
Category: otc | Type: HUMAN OTC DRUG LABEL
Date: 20241010

ACTIVE INGREDIENTS: POVIDONE-IODINE 1 mg/10 mL
INACTIVE INGREDIENTS: CITRIC ACID MONOHYDRATE; SODIUM PHOSPHATE, DIBASIC, ANHYDROUS; GLYCERIN; WATER; SODIUM CITRATE; POLYSORBATE 80

Drug Facts

Active Ingredient

Povidone-Iodine, 10% (equivalent to 1% available Iodine)

Purpose

Antiseptic

Uses

- Health-care antiseptic preparation of the skin prior to surgery.
- First aid antiseptic to help prevent infection in minor cuts, scrapes and burns.

Warnings

For external use only

Do not

- use in the eyes
- use as a first aid antiseptic Longer than one week
- use on individuals who are allergic or sensitive to iodine
- use on deep or puncture wounds
- use on animal bites
- use on serious burns
- apply over Large areas of the body

Stop use and ask a doctor if

- conditions persists or gets worse
- irritation and redness develop and persists for more than 72 hours

Keep out of the reach of children.

If swallowed, get medical help or contact a Poison Control Center right away.

Directions

For preparation of the skin prior to surgery

- Apply product to the operative site prior to surgery

As a first aid antiseptic

- Clean the affected area
- Apply a small amount of this product on the area 1-3 times daily
- May be covered with a sterile bandage
- If bandaged, Let dry first

Other Information

- Do not store above 77°F (25°C)
- Do not store below 68°F (20°C)

Not made with natural rubber latex.

Inactive ingredient

Citric Acid, Disodium Phosphate, Glycerin, Purified Water, Sodium Citrate, Tween 80

Principal Display Panel - McKesson PVP Prep Solution 4 fl oz Carton label

NDC 68599-3502-1

McKESSON

PVP Prep Solution
MFR# 039
USP 10%

POVIDONE IODINE

TOPICAL ANTISEPTIC MICROBICIDE

NET CONTENTS

4 fl oz

(118 mL)

Principal Display Panel - McKesson PVP Prep Solution 4 fl oz label

NDC 68599-3502-2

McKESSON

PVP Prep Solution USP

10% POVIDONE IODINE

NET CONTENTS

4 fl oz (118 mL)

36 BOTTLES PER CASE

Do not store above 77°F (25°C).

Do not store below 68°F (20°C).

Not made with natural rubber latex.

Distributed By

McKesson Medical-Surgical Inc.

Richmond. VA 23233

PVN B0520 Made in Mexico

LOT

EXP

MFR# 039

Principal Display Panel - McKesson PVP Prep Solution 16 fl oz Carton label

NDC 68599-3500-1

McKESSON

PVP Prep Solution USP
10% POVIDONE IODINE

TOPICAL ANTISEPTIC MICROBICIDE

NET CONTENTS

16 fl oz

(473 mL)

MFR# 035

Principal Display Panel - McKesson PVP Prep Solution 16 fl oz label

NDC 68599-3500-2

McKESSON

PVP Prep Solution USP

10% POVIDONE IODINE

NET CONTENTS

16 fl oz (473 mL)

12 BOTTLES PER CASE

Do not store above 77°F (25°C).

Do not store below 68°F (20°C).

Not made with natural rubber latex.

Distributed By

McKesson Medical-Surgical Inc.

Richmond. VA 23233

PVN B0520 Made in Mexico

LOT

EXP

MFR# 035

Principal Display Panel - McKesson PVP Prep Solution 1 gal Carton label

NDC 68599-3500-5

McKESSON

PVP Prep Solution USP

10% POVIDONE IODINE

TOPICAL ANTISEPTIC MICROBICIDE

NET CONTENTS

1 gal

(3.8 L)

MFR# 036

Principal Display Panel - McKesson PVP Prep Solution 1 gal label

NDC 68599-3500-6

McKESSON

PVP Prep Solution USP

10% POVIDONE IODINE

NET CONTENTS

1 gal (3.8 L)

4 BOTTLES PER CASE

Do not store above 77°F (25°C).

Do not store below 68°F (20°C).

Not made with natural rubber latex.

Distributed By

McKesson Medical-Surgical Inc.

Richmond. VA 23233

PNV B0520 Made in Mexico

LOT

EXP

MFR# 036

Principal Display Panel - McKesson PVP Prep Solution 8 fl oz. label

NDC 68599-3502-5

McKESSON

PVP Prep Solution
USP 10%

POVIDONE IODINE

TOPICAL ANTISEPTIC MICROBICIDE

NET CONTENTS

8 fl oz

(237 mL)

MFR # 034

Principal Display Panel - McKesson PVP Prep Solution 8 fl. oz. Carton Label

NDC 68599-3502-6

McKESSON

PVP Prep Solution USP

10% POVIDONE IODINE

NET CONTENTS

8 fl oz (237 mL)

24 BOTTLES PER CASE

Do not store above 77°F (25°C).

Do not store below 68°F (20°C).

Not made with natural rubber latex.

Distributed By

McKesson Medical-Surgical Inc.

Richmond. VA 23233

PVN B0520 Made in Mexico

LOT

EXP

MFR# 034